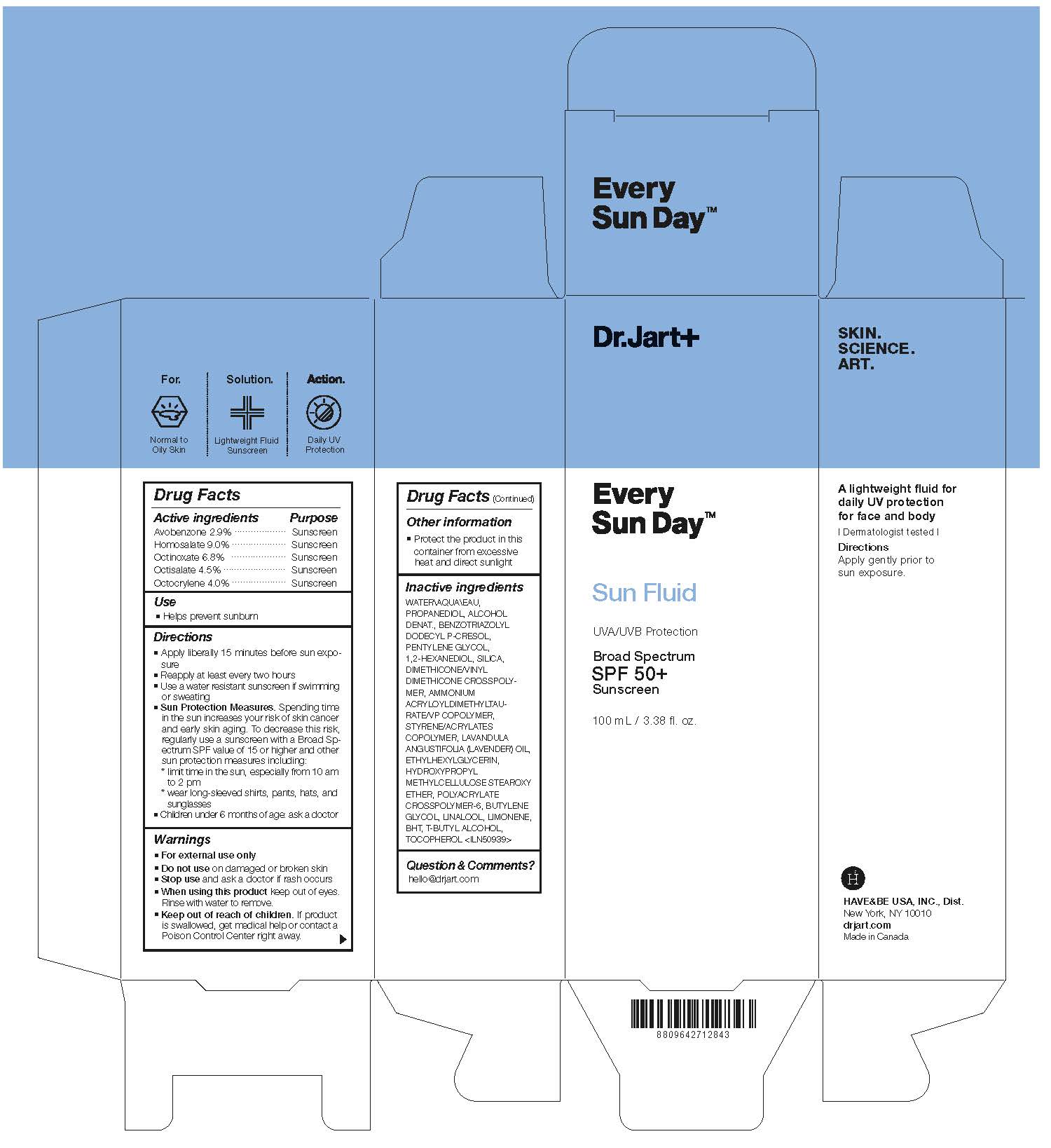 DRUG LABEL: DR.JART EVERY SUN DAY SUN FLUID
NDC: 49404-307 | Form: LIQUID
Manufacturer: Have & Be Co., Ltd.
Category: otc | Type: HUMAN OTC DRUG LABEL
Date: 20250206

ACTIVE INGREDIENTS: OCTOCRYLENE 40 mg/1 mL; HOMOSALATE 90 mg/1 mL; OCTINOXATE 68 mg/1 mL; AVOBENZONE 29 mg/1 mL; OCTISALATE 45 mg/1 mL
INACTIVE INGREDIENTS: PROPANEDIOL; LAVENDER OIL; 1,2-HEXANEDIOL; BUTYLENE GLYCOL; LIMONENE, (+)-; LINALOOL, (+/-)-; PENTYLENE GLYCOL; ALCOHOL; DIMETHICONE/VINYL DIMETHICONE CROSSPOLYMER (HARD PARTICLE); TERT-BUTYL ALCOHOL; TOCOPHEROL; HYPROMELLOSE 2208 0.45% STEAROXY ETHER; SILICON DIOXIDE; BENZOTRIAZOLYL DODECYL P-CRESOL; BUTYLATED HYDROXYTOLUENE; ETHYLHEXYLGLYCERIN; AMMONIUM ACRYLOYLDIMETHYLTAURATE, DIMETHYLACRYLAMIDE, LAURYL METHACRYLATE AND LAURETH-4 METHACRYLATE COPOLYMER, TRIMETHYLOLPROPANE TRIACRYLATE CROSSLINKED (45000 MPA.S); AMMONIUM ACRYLOYLDIMETHYLTAURATE/VP COPOLYMER; WATER; BUTYL METHACRYLATE/METHYL METHACRYLATE/METHACRYLIC ACID/STYRENE CROSSPOLYMER

DR.JART EVERY SUN DAY SUN FLUID

Active ingredients

Avobenzone 2.9%
Homosalate 9.0%
Octinoxate 6.8%
Octisalate 4.5%
Octocrylene 4.0%

Purpose

Sunscreen

Use

Helps prevent sunburn

Warnings

For external use only

Do not use

on damaged or broken skin

When using this product

keep out of eyes. Rinse with water to remove.

Stop use

and ask a doctor if rash occurs

Keep out of reach of children.

If productis swallowed, get medical help or contact a Poison Control Center right away.

Directions

■ Apply liberally 15 minutes before sun exposure
■ Reapply at least every two hours
■ Use a water resistant sunscreen if swimming
or sweating
■ Sun Protection Measures. Spending time
in the sun increases your risk of skin cancer
and early skin aging. To decrease this risk,
regularly use a sunscreen with a Broad Spectrum
SPF value of 15 or higher and other
sun protection measures including:
* limit time in the sun, especially from 10 am
to 2 pm
* wear long-sleeved shirts, pants, hats, and
sunglasses
■ Children under 6 months of age: ask a doctor

Inactive ingredients

WATER\AQUA\EAU,
PROPANEDIOL, ALCOHOL
DENAT., BENZOTRIAZOLYL
DODECYL P-CRESOL,
PENTYLENE GLYCOL,
1,2-HEXANEDIOL, SILICA,
DIMETHICONE/VINYL
DIMETHICONE CROSSPOLYMER,
AMMONIUM
ACRYLOYLDIMETHYLTAURATE/
VP COPOLYMER,
STYRENE/ACRYLATES
COPOLYMER, LAVANDULA
ANGUSTIFOLIA (LAVENDER) OIL,
ETHYLHEXYLGLYCERIN,
HYDROXYPROPYL
METHYLCELLULOSE STEAROXY
ETHER, POLYACRYLATE
CROSSPOLYMER-6, BUTYLENE
GLYCOL, LINALOOL, LIMONENE,
BHT, T-BUTYL ALCOHOL,
TOCOPHEROL <ILN50939>

Other information

Protect the product in this
container from excessive
heat and direct sunlight

PACKAGE LABEL

Every Sun Day
Sun Fluid

UVA/UVB Protection

Broad Spectrum

SPF 50+

100 mL / 3.38 fl. oz.